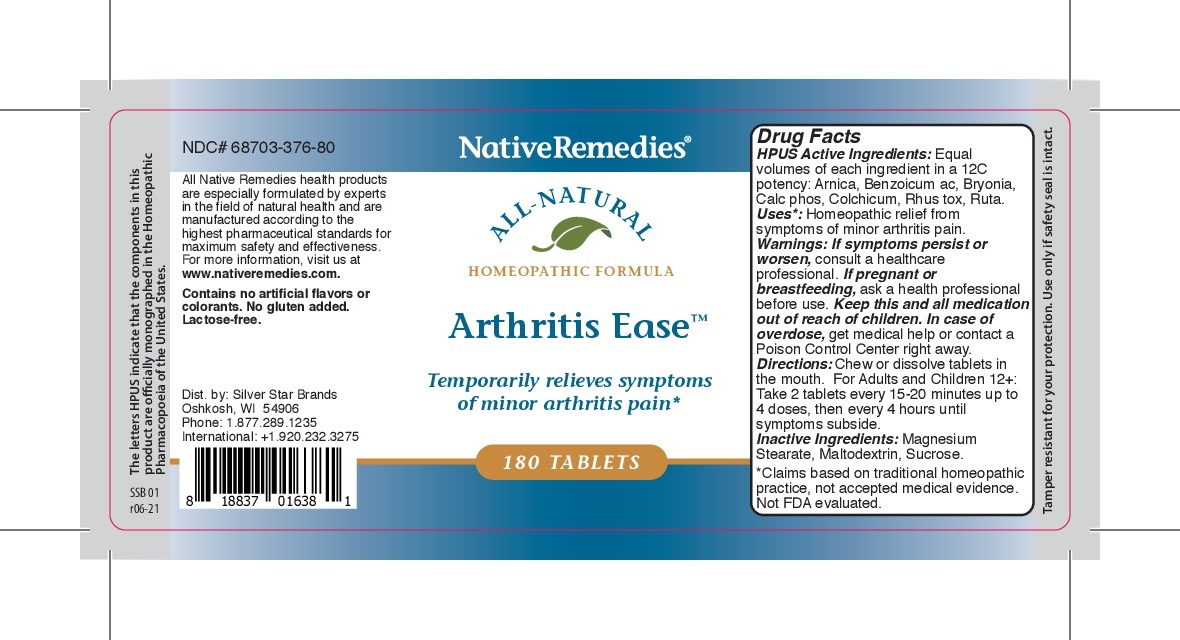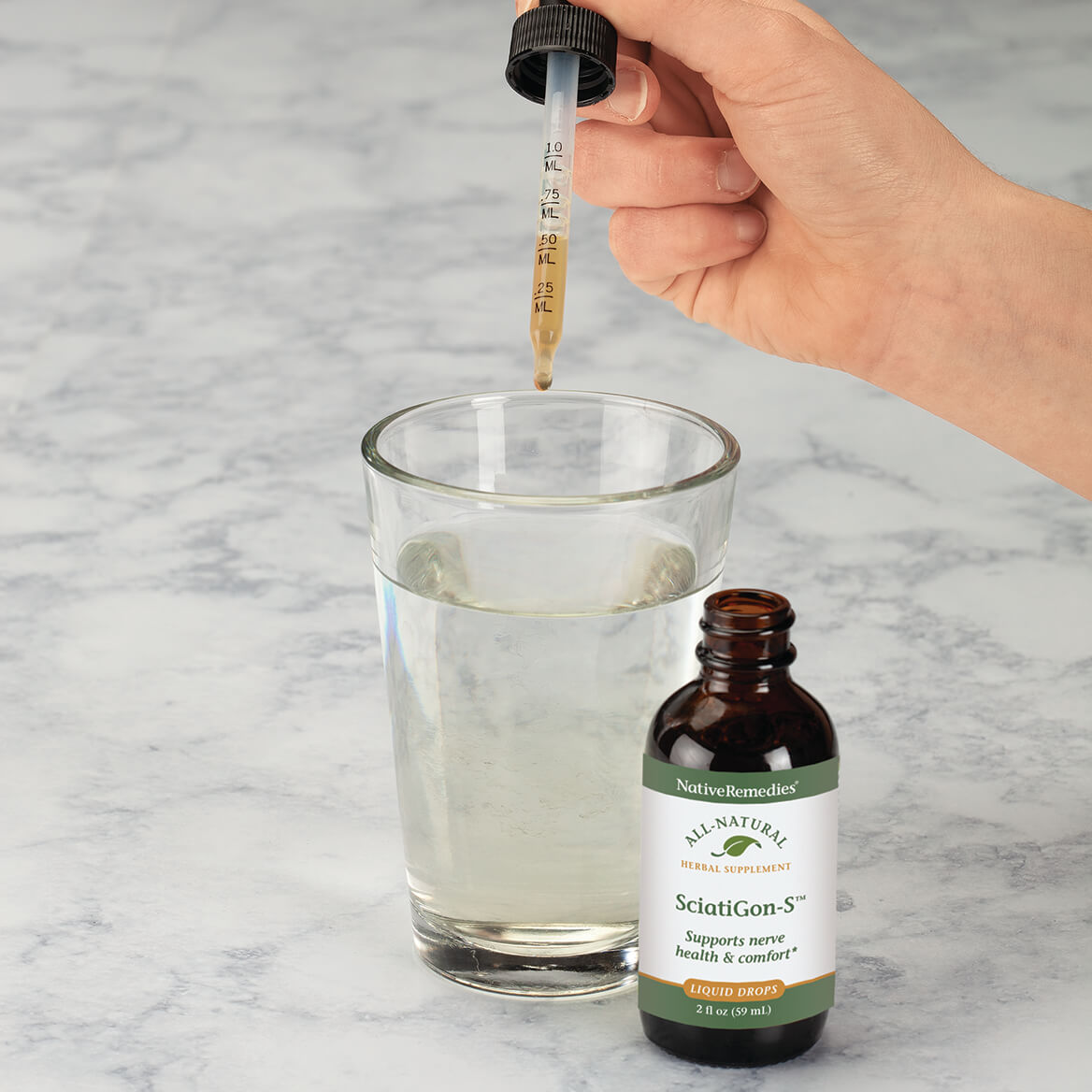 DRUG LABEL: Arthritis Ease
NDC: 68703-376 | Form: TABLET
Manufacturer: Silver Star Brands
Category: homeopathic | Type: HUMAN OTC DRUG LABEL
Date: 20250101

ACTIVE INGREDIENTS: BENZOIC ACID 12 [hp_C]/180 1; BRYONIA ALBA ROOT 12 [hp_C]/180 1; ARNICA MONTANA 12 [hp_C]/180 1; TOXICODENDRON RADICANS LEAF 12 [hp_C]/180 1; CALCIUM PHOSPHATE 12 [hp_C]/180 1; COLCHICUM AUTUMNALE BULB 12 [hp_C]/180 1; RUTA GRAVEOLENS FLOWERING TOP 12 [hp_C]/180 1
INACTIVE INGREDIENTS: SUCROSE; MAGNESIUM STEARATE; MALTODEXTRIN

NativeRemedies® Arthritis Ease Tablets

HPUS Active Ingredients: Equal volumes of each ingredient ina 12C potency: Arnica, Benzoicum ac, Bryonia, Calc phos, Colchicum, Rhus tox, Ruta.

Uses*

Uses*: Homeopathic relief from symptoms of minor arthritis pain.

*Claims based on traditional homeopathic practice, not accepted medical evidence. Not FDA evaluated.

Warnings

Warnings: If symptoms persist or worsen, consult a healthcare professional. Keep this and all medication out of reach of children. In case of overdose, get medical help or contact a Poison Control Center right away.

Directions

Directions: Chew or dissolve tablets in the mouth. For Adults and Children 12+: Take 2 tablets every 15-20 minutes up to 4 doses, then every 4 hours until symptoms subside.

OTHER SAFETY INFORMATION

Contains no artificial flavors or colorants. No gluten added. Lactose-free.

Tamper resistant for your protection. Use only if safety seal is intact.

Inactive Ingredients

Inactive Ingredients: Magnesium Stearate, Maltodextrin, Sucrose.

KEEP OUT OF REACH OF CHILDREN

Keep this and all medication out of reach of children.

PREGNANCY OR BREAST FEEDING

If pregnant or breastfeeding, ask a health professional before use.

PURPOSE

Temporarily relieves symptoms of minor arthritis pain*

*Claims based on traditional homeopathic practice, not accepted medical evidence. Not FDA evaluated.